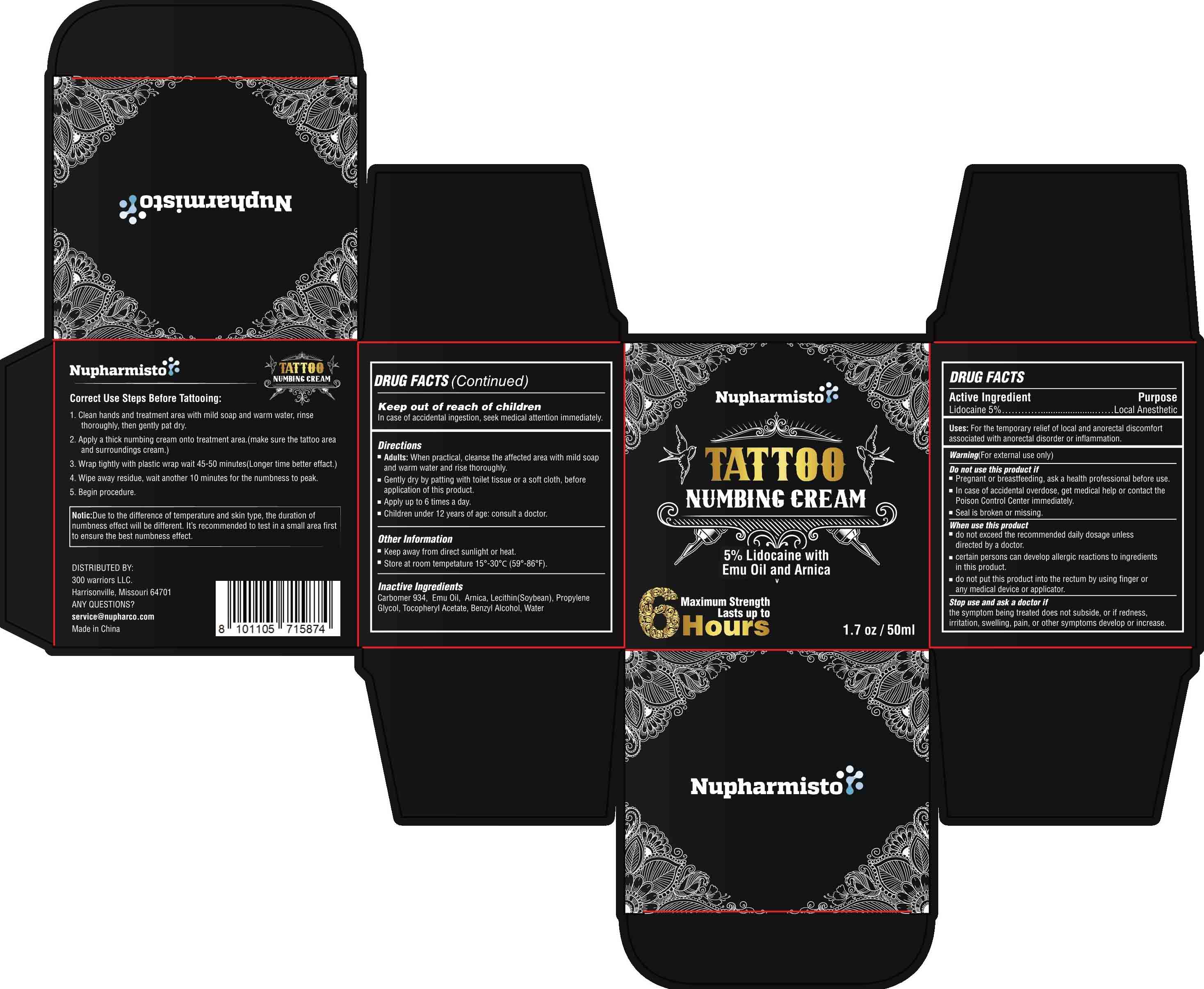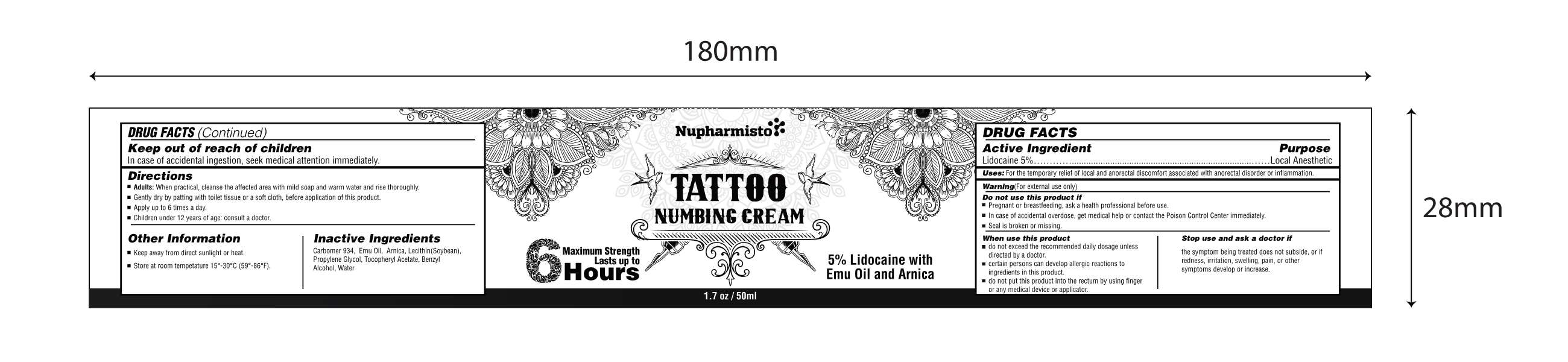 DRUG LABEL: Nupharmisto Tattoo Numbing Cream
NDC: 81799-008 | Form: CREAM
Manufacturer: Ehy Holdings LLC
Category: otc | Type: HUMAN OTC DRUG LABEL
Date: 20230215

ACTIVE INGREDIENTS: LIDOCAINE 5 mg/100 mL
INACTIVE INGREDIENTS: BENZYL ALCOHOL; WATER; CARBOXYPOLYMETHYLENE; PROPYLENE GLYCOL; .ALPHA.-TOCOPHEROL ACETATE, DL-; LECITHIN, SOYBEAN

81799-008
Nupharmisto Tattoo Numbing Cream

Active Ingredient(s)

Lidocaine 5%

Purpose

Local Anesthetic

Use

For the temporary relief of local and anorectal discomfort associated with anorectal disorder or inflammation.

Warnings

For external use only

Do not use

Pregnant or breastfeeding, ask a health professional before use.
In case of accidental overdose, get medical help or contact the
Poison Control Center immediately.
Seal is broken or missing

WHEN USING

directed by a doctor.
certain persons can develop allergic reactions to ingredients
in this product.
do not put this product into the rectum by using finger or
any medical device or applicator

STOP USE

the symptom being treated does not subside, or if redness

KEEP OUT OF REACH OF CHILDREN

Adults: When practical, cleanse the affected area with mild soap
and warm water and rise thoroughly.
Gently dry by patting with toilet tissue or a soft cloth, before
application of this product.
Apply up to 6 times a day.
Children under 12 years of age: consult a doctor

Directions

Adults: When practical, cleanse the affected area with mild soap
and warm water and rise thoroughly.
Gently dry by patting with toilet tissue or a soft cloth, before
application of this product.
Apply up to 6 times a day.
Children under 12 years of age: consult a doctor

Other information

Keep away from direct sunlight or heat.
Store at room tempetature 15°-30°C (59°-86°F)

Inactive ingredients

Carbomer 934, Emu Oil, Arnica, Lecithin(Soybean), Propylene
Glycol, Tocopheryl Acetate, Benzyl Alcohol, Water

ASK DOCTOR

irritation, swelling, pain, or other symptoms develop or increase

QUESTIONS

service@nupharco.com

Package Label - Principal Display Panel

81799-008-01 1

81799-008-01 2